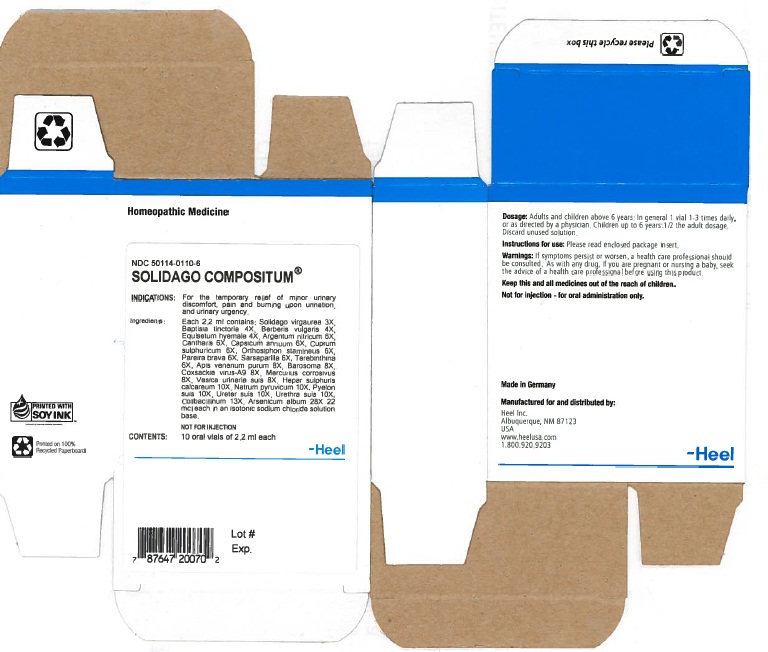 DRUG LABEL: Solidago Compositum
NDC: 50114-0110 | Form: SOLUTION
Manufacturer: Heel Inc
Category: homeopathic | Type: HUMAN OTC DRUG LABEL
Date: 20120510

ACTIVE INGREDIENTS: SOLIDAGO VIRGAUREA FLOWERING TOP 3 [hp_X]/2.2 mL; BAPTISIA TINCTORIA ROOT 4 [hp_X]/2.2 mL; BERBERIS VULGARIS ROOT BARK 4 [hp_X]/2.2 mL; EQUISETUM HYEMALE 4 [hp_X]/2.2 mL; SILVER NITRATE 6 [hp_X]/2.2 mL; LYTTA VESICATORIA 6 [hp_X]/2.2 mL; CAPSICUM 6 [hp_X]/2.2 mL; CUPRIC SULFATE 6 [hp_X]/2.2 mL; CLERODENDRANTHUS SPICATUS LEAF 6 [hp_X]/2.2 mL; CHONDRODENDRON TOMENTOSUM ROOT 6 [hp_X]/2.2 mL; SMILAX REGELII ROOT 6 [hp_X]/2.2 mL; TURPENTINE OIL 6 [hp_X]/2.2 mL; APIS MELLIFERA VENOM 8 [hp_X]/2.2 mL; AGATHOSMA BETULINA LEAF 8 [hp_X]/2.2 mL; HUMAN COXSACKIEVIRUS A 8 [hp_X]/2.2 mL; MERCURIC CHLORIDE 8 [hp_X]/2.2 mL; SUS SCROFA URINARY BLADDER 8 [hp_X]/2.2 mL; CALCIUM SULFIDE 10 [hp_X]/2.2 mL; SODIUM PYRUVATE 10 [hp_X]/2.2 mL; SUS SCROFA RENAL PELVIS 10 [hp_X]/2.2 mL; SUS SCROFA URETER 10 [hp_X]/2.2 mL; SUS SCROFA URETHRA 10 [hp_X]/2.2 mL; ESCHERICHIA COLI 13 [hp_X]/2.2 mL; ARSENIC TRIOXIDE 28 [hp_X]/2.2 mL
INACTIVE INGREDIENTS: SODIUM CHLORIDE

Solidago Compositum 2.2ml Oral Vial

ACTIVE INGREDIENTS

Active ingredients: Each 2.2 ml contains: Solidago virgaurea 3X, Baptisia tinctoria 4X, Berberis vulgaris 4X, Equisetum hyemale 4X, Argentum nitricum 6X, Cantharis 6X, Capsicum annuum 6X, Cuprum sulphuricum 6X, Orthosiphon stamineus 6X, Pareira brava 6X, Sarsaparilla 6X, Terebinthina 6X, Apis venenum purum 8X, Barosoma 8X, Coxsackie virus-A9 8X, Mercurius corrosivus 8X, Vesica urinaria suis 8X, Hepar sulphuris calcareum 10X, Natrum pyruvicum 10X, Pyelon suis 10X, Ureter suis 10X, Urethra suis 10X, Colibacillinum 13X, Arsenicum album 28X 22 mcl each.

PURPOSE

Minor urinary discomfort, Pain and burning upon urination, Urinary urgency

KEEP OUT OF REACH OF CHILDREN

Keep this and all medicines out of the reach of children.

INDICATIONS AND USAGE

Indications: For the temporary relief of:

- Minor urinary discomfort
- Pain and burning upon urination
- Urinary urgency.

WARNINGS

Warnings: If symptoms persist or worsen, a health care professional should be consulted. As with any drug, if you are pregnant or nursing a baby, seek the advise of a health care professional before using this product.

DOSAGE AND ADMINISTRATION

Dosasge: Adults and children above 6 years: In general 1 vial 1 - 3 times daily, or as directed by a physician. Children up to 6 years: 1/2 the adult dosage. Discard unused solution.

INACTIVE INGREDIENTS

Inactive ingredients: Isotonic sodium chloride solution